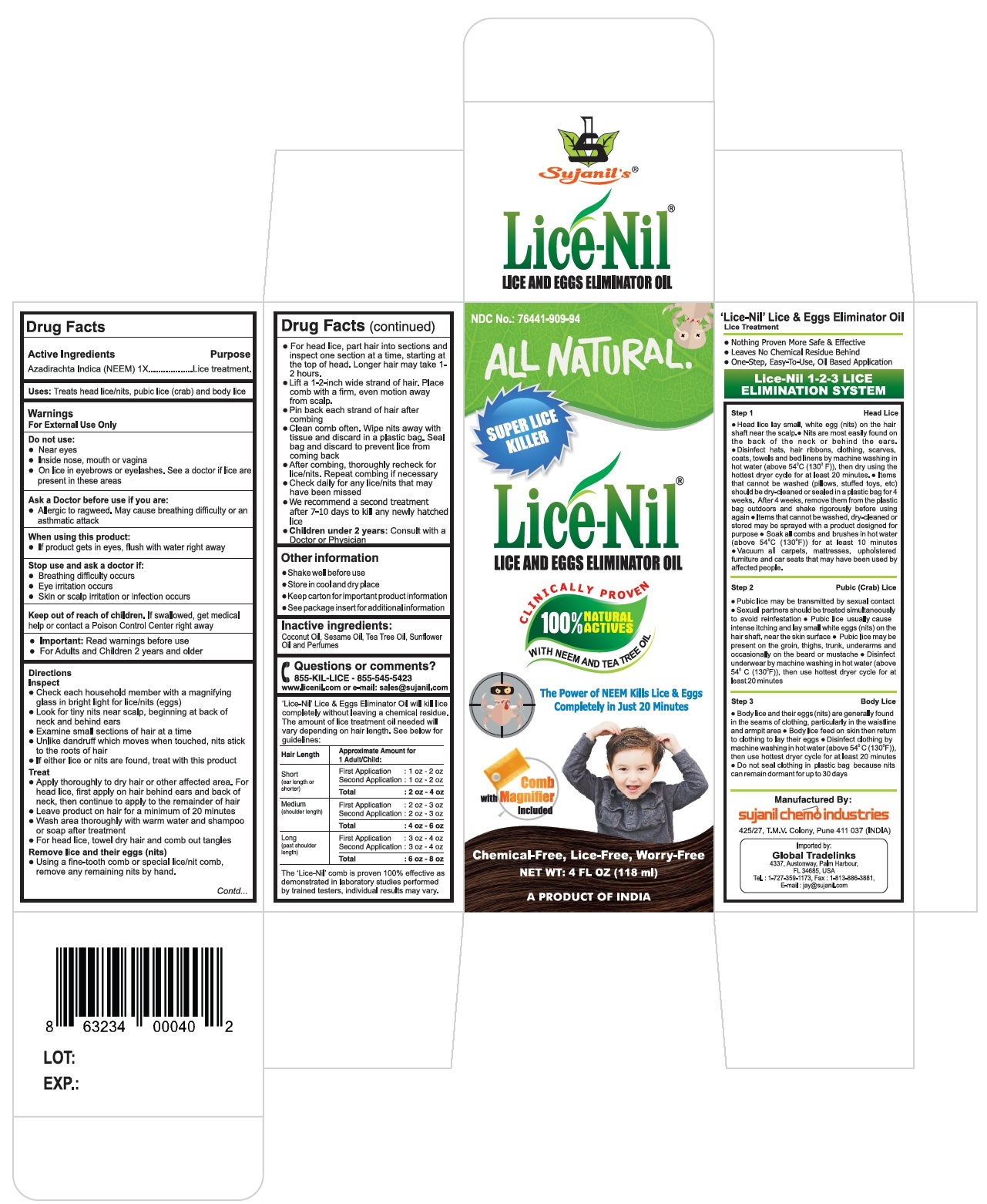 DRUG LABEL: Lice-Nil LICE AND EGGS ELIMINATOR Oil
NDC: 76441-909 | Form: OIL
Manufacturer: Sujanil Chemo Industries
Category: homeopathic | Type: HUMAN OTC DRUG LABEL
Date: 20170824

ACTIVE INGREDIENTS: AZADIRACHTA INDICA SEED OIL 1 [hp_X]/100 mL
INACTIVE INGREDIENTS: COCONUT OIL; SESAME OIL; TEA TREE OIL; SUNFLOWER OIL; .ALPHA.-TOCOPHEROL; LAVENDER OIL; JUNIPERUS VIRGINIANA OIL; LEMON OIL; ROSEMARY OIL

Lice-Nil LICE AND EGGS ELIMINATOR OIL

Active Ingredients

Azadirachta Indica (NEEM) 1X

Purpose

Lice treatment.

Uses:

Treats head lice/nits, pubic lice (crab) and body lice

Warnings

For External Use Only

Do not use:

- Near eyes
- Inside nose, mouth or vagina
- On lice in eyebrows or eyelashes. See a doctor if lice are present in these areas

Ask a Doctor before use if you are:

- Allergic to ragweed. May cause breathing difficulty or an asthmatic attack

When using this product:

- If product gets in eyes, flush with water right away

Stop use and ask a doctor if:

- Breathing difficulty occurs
- Eye irritation occurs
- Skin or scalp irritation or infection occurs

Keep out of reach of children. If swallowed, get medical help or contact a Poison Control Center right away

- Important: Read warnings before use
- For Adults and Children 2 years and older

Directions

Inspect

- Check each household member with a magnifying glass in bright light for lice/nits (eggs)
- Look for tiny nits near scalp, beginning at back of neck and behind ears
- Examine small sections of hair at a time
- Unlike dandruff which moves when touched, nits stick to the roots of hair
- If either lice or nits are found, treat with this product

Treat

- Apply thoroughly to dry hair or other affected area. For head lice, first apply on hair behind ears and back of neck, then continue to apply to the remainder of hair
- Leave product on hair for a minimum of 20 minutes
- Wash area thoroughly with warm water and shampoo or soap after treatment
- For head lice, towel dry hair and comb out tangles

Remove lice and their eggs (nits)

- Using a fine-tooth comb or special lice/nit comb, remove any remaining nits by hand.
- For head lice, part hair into sections and inspect one section at a time, starting at the top of head. Longer hair may take 1-2 hours.
- Lift a 1-2-inch wide strand of hair. Place comb with a firm, even motion away from scalp.
- Pin back each strand of hair after combing
- Clean comb often. Wipe nits away with tissue and discard in a plastic bag. Seal bag and discard to prevent lice from coming back
- After combing, thoroughly recheck for lice/nits. Repeat combing if necessary
- Check daily for any lice/nits that may have been missed
- We recommend a second treatment after 7-10 days to kill any newly hatched lice
- Children under 2 years: Consult with a Doctor or Physician

Other information

- Shake well before use
- Store in cool and dry place
- Keep carton for important product information
- See package insert for additional information

Inactive ingredients:

Coconut Oil, Sesame Oil, Tea Tree Oil, Sunflower Oil with Herbal Extracts and Perfumes

Questions or comments?

855-KIL-LICE - 855-545-5423

www.licenil.com or e-mail: sales@sujanil.com

'Lice-Nil' Lice & Eggs Eliminator Oil will kill lice completely without leaving a chemical residue. The amount of lice treatment oil needed will vary depending on hair length. See below for guidelines:

Hair Length | Approximate Amount for 1 Adult/Child:
Short | First Application | : 1 oz - 2 oz
(ear length or shorter) | Second Application | : 1 oz - 2 oz
 | Total | : 2 oz - 4 oz
Medium | First Application | : 2 oz - 3 oz
(shoulder length) | Second Application | : 2 oz - 3 oz
 | Total | : 4 oz - 6 oz
Long | First Application | : 3 oz - 4 oz
(past shoulder length) | Second Application | : 3 oz - 4 oz
 | Total | : 6 oz - 8 oz

The 'Lice-Nil' comb is proven 100% effective as demonstrated in laboratory studies performed by trained testers, individual results may vary.

'Lice-Nil' Lice & Eggs Eliminator Oil

Lice Treatment

- Nothing Proven More Safe & Effective
- Leaves No Chemical Residue Behind
- One-Step, Easy-To-Use, Oil Based Application

Lice-Nil 1-2-3 LICE ELIMINATION SYSTEM

Step 1 Head Lice

- Head lice lay small, white eggs (nits) on the hair shaft near the scalp.
- Nits are most easily found on the back of the neck or behind the ears.
- Disinfect hats, hair ribbons, clothing, scarves, coats, towels and bed linens by machine washing in hot water (above 54°C (130°F)), then dry using the hottest dryer cycle for at least 20 minutes.
- Items that cannot be washed (pillows, stuffed toys, etc.) should be dry-cleaned or sealed in a plastic bag for 4 weeks. After 4 weeks, remove them from the plastic bag outdoors and shake rigorously before using again
- Items that cannot be washed, dry-cleaned or stored may be sprayed with a product designed for purpose
- Soak all combs and brushes in hot water (above 54°C (130°F)) for at least 10 minutes
- Vacuum all carpets, mattresses, upholstered furniture and car seats that may have been used by affected people.

Step 2 Pubic (Crab) Lice

- Pubic lice may be transmitted by sexual contact
- Sexual partners should be treated simultaneously to avoid reinfestation
- Pubic lice usually cause intense itching and lay small white eggs (nits) on the hair shaft, near the skin surface
- Pubic lice may be present on the groin, thighs, trunk, underarms and occasionally on the beard and mustache
- Disinfect underwear by machine washing in hot water (above 54°C (130°F)), then use hottest dryer cycle for at least 20 minutes

Step 3 Body Lice

- Body lice and their eggs (nits) are generally found in the seams of clothing, particularly in the waistline and armpit area
- Body lice feed on skin then return to clothing to lay their eggs
- Disinfect clothing by machine washing in hot water (above 54°C (130°F)), then use hottest dryer cycle for at least 20 minutes
- Do not seal clothing in plastic bag because nits can remain dormant for up to 30 days

ALL NATURAL

SUPER LICE KILLER

CLINICALLY PROVEN

100% NATURAL ACTIVES

WITH NEEM AND TEA TREE OIL

The Power of NEEM Kills Lice & Eggs Completely in Just 20 Minutes

Comb with Magnifier Included

Chemical-Free, Lice-Free, Worry-Free

A PRODUCT OF INDIA

Manufactured By:

sujanil chemo industries

425/27, T.M.V. Colony, Pune 411 037 (INDIA)

Imported by:

Global Tradelinks

4337, Austonway, Palm Harbour,

FL 34685, USA

Tel. : 1-727-359-1173, Fax : 1-813-886-3881,

E-mail : jay@sujanil.com